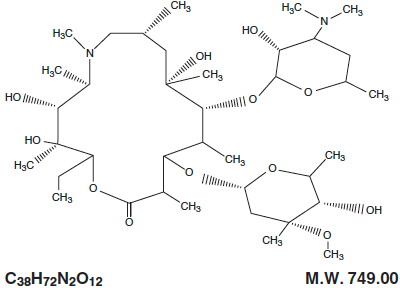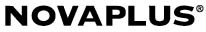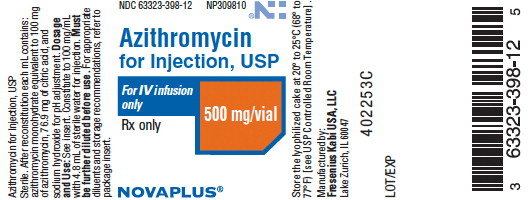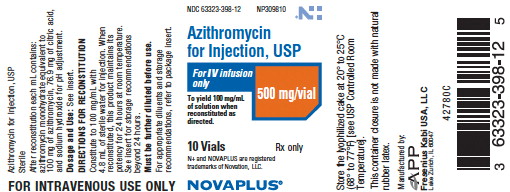 DRUG LABEL: Azithromycin
NDC: 63323-398 | Form: INJECTION, POWDER, LYOPHILIZED, FOR SOLUTION
Manufacturer: Fresenius Kabi USA, LLC
Category: prescription | Type: HUMAN PRESCRIPTION DRUG LABEL
Date: 20241011

ACTIVE INGREDIENTS: AZITHROMYCIN MONOHYDRATE 500 mg/5 mL
INACTIVE INGREDIENTS: SODIUM HYDROXIDE; CITRIC ACID MONOHYDRATE

Azithromycin for Injection, USP

For IV infusion only

Rx only

To reduce the development of drug-resistant bacteria and maintain the effectiveness of Azithromycin for Injection and other antibacterial drugs, Azithromycin for Injection should be used only to treat or prevent infections that are proven or strongly suspected to be caused by bacteria.

DESCRIPTION

Azithromycin for Injection, USP contains the active ingredient azithromycin, an azalide, a subclass of macrolide antibiotics, for intravenous injection. Azithromycin has the chemical name (2R,3S,4R,5R,8R,10R,11R,12S,13S,14R)-13-[(2,6-dideoxy-3- C-methyl-3- O-methyl-α- L- ribo-hexopyranosyl)oxy]-2-ethyl-3,4,10-trihydroxy-3,5,6,8,10,12,14-heptamethyl-11-[[3,4,6-trideoxy-3-(dimethylamino)-β- D-xylo-hexopyranosyl]oxy]-1-oxa-6-azacyclopentadecan-15-one. Azithromycin is derived from erythromycin; however, it differs chemically from erythromycin in that a methyl-substituted nitrogen atom is incorporated into the lactone ring. Azithromycin has the following structural formula:

Azithromycin, as the monohydrate, is a white crystalline powder with a molecular formula of C38H72N2O12•H2O and a molecular weight of 767.00.

Azithromycin for Injection, USP consists of azithromycin monohydrate and the following inactive ingredients: citric acid and sodium hydroxide. Azithromycin for Injection, USP is supplied in lyophilized form in a 10 mL vial equivalent to 500 mg of azithromycin for intravenous administration. Reconstitution, according to label directions, results in approximately 5 mL of azithromycin for intravenous injection with each mL containing azithromycin monohydrate equivalent to 100 mg of azithromycin. After reconstitution each mL contains: azithromycin monohydrate equivalent to 100 mg of azithromycin, 76.9 mg of citric acid, and sodium hydroxide for pH adjustment.

CLINICAL PHARMACOLOGY

Pharmacokinetics

In patients hospitalized with community-acquired pneumonia receiving single daily one-hour intravenous infusions for 2 to 5 days of 500 mg azithromycin at a concentration of 2 mg/mL, the mean Cmax ± S.D. achieved was 3.63 ± 1.6 mcg/mL, while the 24-hour trough level was 0.2 ± 0.15 mcg/mL, and the AUC24 was 9.6 ± 4.8 mcg•h/mL.

The mean Cmax, 24-hour trough and AUC24 values were 1.14 ± 0.14 mcg/mL, 0.18 ± 0.02 mcg/mL, and 8.03 ± 0.86 mcg•h/mL, respectively, in normal volunteers receiving a 3-hour intravenous infusion of 500 mg azithromycin at a concentration of 1 mg/mL. Similar pharmacokinetic values were obtained in patients hospitalized with community-acquired pneumonia who received the same 3-hour dosage regimen for 2 to 5 days.

Plasma concentrations (mcg/mL ± S.D.) after the last daily intravenous infusion of 500 mg azithromycin
Infusion Concentration, Duration | Time after starting the infusion (hr)
 | 0.5 | 1 | 2 | 3 | 4 | 6 | 8 | 12 | 24
2 mg/mL, 1 hra | 2.98 ± 1.12 | 3.63 ± 1.73 | 0.6 ± 0.31 | 0.4 ± 0.23 | 0.33 ± 0.16 | 0.26 ± 0.14 | 0.27 ± 0.15 | 0.2 ± 0.12 | 0.2 ± 0.15
1 mg/mL, 3 hrb | 0.91 ± 0.13 | 1.02 ± 0.11 | 1.14 ± 0.13 | 1.13 ± 0.16 | 0.32 ± 0.05 | 0.28 ± 0.04 | 0.27 ± 0.03 | 0.22 ± 0.02 | 0.18 ± 0.02

a = 500 mg (2 mg/mL) for 2 to 5 days in community-acquired pneumonia patients.

b = 500 mg (1 mg/mL) for 5 days in healthy subjects.

The average CLt and Vd values were 10.18 mL/min/kg and 33.3 L/kg, respectively, in 18 normal volunteers receiving 1000 to 4000 mg doses given as 1 mg/mL over 2 hours.

Comparison of the plasma pharmacokinetic parameters following the 1st and 5th daily doses of 500 mg intravenous azithromycin showed only an 8% increase in Cmax but a 61% increase in AUC24 reflecting a threefold rise in C24 trough levels.

Following single oral doses of 500 mg azithromycin (two 250 mg capsules) to 12 healthy volunteers, Cmax, trough level, and AUC24 were reported to be 0.41 mcg/mL, 0.05 mcg/mL, and 2.6 mcg•h/mL, respectively. These oral values are approximately 38%, 83%, and 52% of the values observed following a single 500 mg IV 3-hour infusion (Cmax: 1.08 mcg/mL, trough: 0.06 mcg/mL, and AUC24: 5 mcg•h/mL). Thus, plasma concentrations are higher following the intravenous regimen throughout the 24-hour interval. The pharmacokinetic parameters on day 5 of azithromycin 250 mg capsules following a 500 mg oral loading dose to healthy young adults (age 18 to 40 years old) were as follows: Cmax: 0.24 mcg/mL, AUC24: 2.1 mcg•h/mL. Azithromycin 250 mg capsules are no longer commercially available. Azithromycin 250 mg tablets are bioequivalent to 250 mg capsules in the fasting state.

Median azithromycin exposure (AUC0-288) in mononuclear (MN) and polymorphonuclear (PMN) leukocytes following 1,500 mg of oral azithromycin, administered in single daily doses over either 5 days (two 250 mg tablets on day 1, followed by one 250 mg tablet on days 2 to 5) or 3 days (500 mg per day for days 1 to 3) to 12 healthy volunteers, was more than a 1000-fold and 800-fold greater than in serum, respectively.

Distribution

The serum protein binding of azithromycin is variable in the concentration range approximating human exposure, decreasing from 51% at 0.02 mcg/mL to 7% at 2 mcg/mL.

Tissue concentrations have not been obtained following intravenous infusions of azithromycin. Selected tissue (or fluid) concentration and tissue (or fluid) to plasma/serum concentration ratios following oral administration of azithromycin are shown in the following table:

AZITHROMYCIN CONCENTRATIONS FOLLOWING A 500 mg DOSE (TWO 250 mg CAPSULES) IN ADULTS

TISSUE OR FLUID | TIME AFTER DOSE (h) | TISSUE OR FLUID CONCENTRATION (mcg/g or mcg/mL)^1 | CORRESPONDING PLASMA OR SERUM LEVEL (mcg/mL) | TISSUE (FLUID) PLASMA (SERUM) RATIO^1
SKIN | 72 to 96 | 0.4 | 0.012 | 35
LUNG | 72 to 96 | 4 | 0.012 | >100
SPUTUM* | 2 to 4 | 1 | 0.64 | 2
SPUTUM** | 10 to 12 | 2.9 | 0.1 | 30
TONSIL*** | 9 to 18 | 4.5 | 0.03 | >100
TONSIL*** | 180 | 0.9 | 0.006 | >100
CERVIX**** | 19 | 2.8 | 0.04 | 70

^1High tissue concentrations should not be interpreted to be quantitatively related to clinical efficacy. The antimicrobial activity of azithromycin is pH related and appears to be reduced with decreasing pH. However, the extensive distribution of drug to tissues may be relevant to clinical activity.

* Sample was obtained 2 to 4 hours after the first dose.

** Sample was obtained 10 to 12 hours after the first dose.

*** Dosing regimen of 2 doses of 250 mg each, separated by 12 hours.

**** Sample was obtained 19 hours after a single 500 mg dose.

Tissue levels were determined following a single oral dose of 500 mg azithromycin in 7 gynecological patients. Approximately 17 hours after dosing, azithromycin concentrations were 2.7 mcg/g in ovarian tissue, 3.5 mcg/g in uterine tissue, and 3.3 mcg/g in salpinx. Following a regimen of 500 mg on the first day followed by 250 mg daily for 4 days, concentrations in the cerebrospinal fluid were less than 0.01 mcg/mL in the presence of non-inflamed meninges.

Metabolism

In vitro and in vivo studies to assess the metabolism of azithromycin have not been performed.

Elimination

Plasma concentrations of azithromycin following single 500 mg oral and IV doses declined in a polyphasic pattern with a mean apparent plasma clearance of 630 mL/min and terminal elimination half-life of 68 hours. The prolonged terminal half-life is thought to be due to extensive uptake and subsequent release of drug from tissues.

In a multiple-dose study in 12 normal volunteers utilizing a 500 mg (1 mg/mL) one-hour intravenous-dosage regimen for five days, the amount of administered azithromycin dose excreted in urine in 24 hours was about 11% after the 1st dose and 14% after the 5th dose. These values are greater than the reported 6% excreted unchanged in urine after oral administration of azithromycin. Biliary excretion is a major route of elimination for unchanged drug, following oral administration.

Special Populations

Renal Insufficiency

Azithromycin pharmacokinetics were investigated in 42 adults (21 to 85 years of age) with varying degrees of renal impairment. Following the oral administration of a single 1,000 mg dose of azithromycin, mean Cmax and AUC0-120 increased by 5.1% and 4.2%, respectively in subjects with mild to moderate renal impairment (GFR 10 to 80 mL/min) compared to subjects with normal renal function (GFR >80 mL/min). The mean Cmax and AUC0-120 increased 61% and 35%, respectively in subjects with severe renal impairment (GFR <10 mL/min) compared to subjects with normal renal function (GFR >80 mL/min) (see DOSAGE AND ADMINISTRATION).

Hepatic Insufficiency

The pharmacokinetics of azithromycin in subjects with hepatic impairment has not been established.

Gender

There are no significant differences in the disposition of azithromycin between male and female subjects. No dosage adjustment is recommended based on gender.

Geriatric Patients

Pharmacokinetic studies with intravenous azithromycin have not been performed in older volunteers. Pharmacokinetics of azithromycin following oral administration in older volunteers (65 to 85 years old) were similar to those in younger volunteers (18 to 40 years old) for the 5-day therapeutic regimen.

Pediatric Patients

Pharmacokinetic studies with intravenous azithromycin have not been performed in children.

Drug-Drug Interactions

Drug interaction studies were performed with oral azithromycin and other drugs likely to be co-administered. The effects of co-administration of azithromycin on the pharmacokinetics of other drugs are shown in Table 1 and the effects of other drugs on the pharmacokinetics of azithromycin are shown in Table 2.

Co-administration of azithromycin at therapeutic doses had a modest effect on the pharmacokinetics of the drugs listed in Table 1. No dosage adjustment of drugs listed in Table 1 is recommended when co-administered with azithromycin.

Co-administration of azithromycin with efavirenz or fluconazole had a modest effect on the pharmacokinetics of azithromycin. Nelfinavir significantly increased the Cmax and AUC of azithromycin. No dosage adjustment of azithromycin is recommended when administered with drugs listed in Table 2 (see PRECAUTIONS , Drug Interactions).

Table 1. Drug Interactions: Pharmacokinetic Parameters for Co-administered Drugs in the Presence of Azithromycin

Co-administered Drug | Dose of; Co-administered Drug | Dose of; Azithromycin | n | Ratio (with/without azithromycin) of Co-administered Drug Pharmacokinetic Parameters (90% CI); No Effect = 1
Co-administered Drug | Dose of; Co-administered Drug | Dose of; Azithromycin | n | Mean Cmax | Mean AUC
Atorvastatin | 10 mg/day x 8 days | 500 mg/day PO on days 6 to 8 | 12 | 0.83; (0.63 to 1.08) | 1.01; (0.81 to 1.25)
Carbamazepine | 200 mg/day x 2 days, then 200 mg BID x 18 days | 500 mg/day PO for days 16 to 18 | 7 | 0.97; (0.88 to 1.06) | 0.96; (0.88 to 1.06)
Cetirizine | 20 mg/day x 11 days | 500 mg PO on day 7, then 250 mg/day on days 8 to 11 | 14 | 1.03; (0.93 to 1.14) | 1.02; (0.92 to 1.13)
Didanosine | 200 mg PO BID x 21 days | 1,200 mg/day PO on days 8 to 21 | 6 | 1.44; (0.85 to 2.43) | 1.14; (0.83 to 1.57)
Efavirenz | 400 mg/day x 7 days | 600 mg PO on day 7 | 14 | 1.04* | 0.95*
Fluconazole | 200 mg PO single dose | 1,200 mg PO single dose | 18 | 1.04; (0.98 to 1.11) | 1.01; (0.97 to 1.05)
Indinavir | 800 mg TID x 5 days | 1,200 mg PO on day 5 | 18 | 0.96; (0.86 to 1.08) | 0.9; (0.81 to 1)
Midazolam | 15 mg PO on day 3 | 500 mg/day PO x 3 days | 12 | 1.27; (0.89 to 1.81) | 1.26; (1.01 to 1.56)
Nelfinavir | 750 mg TID x 11 days | 1,200 mg PO on day 9 | 14 | 0.9; (0.81 to 1.01) | 0.85; (0.78 to 0.93)
Rifabutin | 300 mg/day x 10 days | 500 mg PO on day 1, then 250 mg/day on days 2 to 10 | 6 | See footnote below | NA
Sildenafil | 100 mg on days 1 and 4 | 500 mg/day PO x 3 days | 12 | 1.16; (0.86 to 1.57) | 0.92; (0.75 to 1.12)
Theophylline | 4 mg/kg IV on days 1, 11, 25 | 500 mg PO on day 7, 250 mg/day on days 8 to 11 | 10 | 1.19; (1.02 to 1.4) | 1.02; (0.86 to 1.22)
Theophylline | 300 mg PO BID x 15 days | 500 mg PO on day 6, then 250 mg/day on days 7 to 10 | 8 | 1.09; (0.92 to 1.29) | 1.08; (0.89 to 1.31)
Triazolam | 0.125 mg on day 2 | 500 mg PO on day 1, then 250 mg/day on day 2 | 12 | 1.06* | 1.02*
Trimethoprim/; Sulfamethoxazole | 160 mg/800 mg/day PO x 7 days | 1,200 mg PO on day 7 | 12 | 0.85; (0.75 to 0.97)/; 0.9; (0.78 to 1.03) | 0.87; (0.8 to 0.95)/; 0.96; (0.88 to 1.03)
Zidovudine | 500 mg/day PO x 21 days | 600 mg/day PO x 14 days | 5 | 1.12; (0.42 to 3.02) | 0.94; (0.52 to 1.7)
Zidovudine | 500 mg/day PO x 21 days | 1,200 mg/day PO x 14 days | 4 | 1.31; (0.43 to 3.97) | 1.3; (0.69 to 2.43)

NA – Not Available

* - 90% Confidence interval not reported

Mean rifabutin concentrations one-half day after the last dose of rifabutin were 60 ng/mL when co-administered with azithromycin and 71 ng/mL when co-administered with placebo.

Table 2. Drug Interactions: Pharmacokinetic Parameters for Azithromycin in the Presence of Co-administered Drugs (see PRECAUTIONS , Drug Interactions)

Co-administered Drug | Dose of; Co-administered Drug | Dose of Azithromycin | n | Ratio (with/without co-administered drug) of Azithromycin Pharmacokinetic Parameters; (90% CI); No Effect = 1
Co-administered Drug | Dose of; Co-administered Drug | Dose of Azithromycin | n | Mean Cmax | Mean AUC
Efavirenz | 400 mg/day x 7 days | 600 mg PO on day 7 | 14 | 1.22; (1.04 to 1.42) | 0.92*
Fluconazole | 200 mg PO single dose | 1,200 mg PO single dose | 18 | 0.82; (0.66 to 1.02) | 1.07; (0.94 to 1.22)
Nelfinavir | 750 mg TID x 11 days | 1,200 mg PO on day 9 | 14 | 2.36; (1.77 to 3.15) | 2.12; (1.8 to 2.5)
Rifabutin | 300 mg/day x 10 days | 500 mg PO on day 1, then 250 mg/day on days 2 to 10 | 6 | See footnote below | NA

NA – Not available

* - 90% Confidence interval not reported

Mean azithromycin concentrations one day after the last dose were 53 ng/mL when co-administered with 300 mg daily rifabutin and 49 ng/mL when co-administered with placebo.

Pharmacodynamics

Cardiac Electrophysiology

QTc interval prolongation was studied in a randomized, placebo-controlled parallel trial in 116 healthy subjects who received either chloroquine (1000 mg) alone or in combination with azithromycin (500 mg, 1000 mg, and 1500 mg once daily). Co-administration of azithromycin increased the QTc interval in a dose- and concentration-dependent manner. In comparison to chloroquine alone, the maximum mean (95% upper confidence bound) increases in QTcF were 5 (10) ms, 7 (12) ms and 9 (14) ms with the co-administration of 500 mg, 1000 mg and 1500 mg azithromycin, respectively.

Microbiology

Azithromycin acts by binding to the 50S ribosomal subunit of susceptible microorganisms and, thus, interfering with microbial protein synthesis. Nucleic acid synthesis is not affected.

Azithromycin concentrates in phagocytes and fibroblasts as demonstrated by in vitro incubation techniques. Using such methodology, the ratio of intracellular to extracellular concentration was >30 after one hour incubation. In vivo studies suggest that concentration in phagocytes may contribute to drug distribution to inflamed tissues.

Azithromycin has been shown to be active against most isolates of the following microorganisms, both in vitro and in clinical infections as described in the INDICATIONS AND USAGE section of the package insert for azithromycin for injection.

Aerobic and facultative gram-positive microorganisms

Staphylococcus aureus

Streptococcus pneumoniae

NOTE: Azithromycin demonstrates cross-resistance with erythromycin-resistant gram-positive strains. Most strains of Enterococcus faecalis and methicillin-resistant staphylococci are resistant to azithromycin.

Aerobic and facultative gram-negative microorganisms

Haemophilus influenzae

Moraxella catarrhalis

Neisseria gonorrhoeae

“Other” microorganisms

Chlamydia pneumoniae

Chlamydia trachomatis

Legionella pneumophila

Mycoplasma hominis

Mycoplasma pneumoniae

Beta-lactamase production should have no effect on azithromycin activity.

Azithromycin has been shown to be active against most strains of the following microorganisms, both in vitro and in clinical infections as described in the INDICATIONS AND USAGE section of the package insert for azithromycin tablets and azithromycin for oral suspension.

Aerobic and facultative gram-positive microorganisms

Staphylococcus aureus

Streptococcus agalactiae

Streptococcus pneumoniae

Streptococcus pyogenes

Aerobic and facultative gram-negative microorganisms

Haemophilus ducreyi

Haemophilus influenzae

Moraxella catarrhalis

Neisseria gonorrhoeae

“Other” microorganisms

Chlamydia pneumoniae

Chlamydia trachomatis

Mycoplasma pneumoniae

Beta-lactamase production should have no effect on azithromycin activity.

The following in vitro data are available, but their clinical significance is unknown.

At least 90% of the following microorganisms exhibit an in vitro minimum inhibitory concentration (MIC) less than or equal to the susceptible breakpoints for azithromycin. However, the safety and effectiveness of azithromycin in treating clinical infections due to these microorganisms have not been established in adequate and well-controlled clinical trials.

Aerobic and facultative gram-positive microorganisms

Streptococci (Groups C, F, G)

Viridans group streptococci

Aerobic and facultative gram-negative microorganisms

Bordetella pertussis

Anaerobic microorganisms

Peptostreptococcus species

Prevotella bivia

“Other” microorganisms

Ureaplasma urealyticum

Beta-lactamase production should have no effect on azithromycin activity.

Susceptibility Testing Methods

When available, the results of in vitro susceptibility test results for antimicrobial drugs used in resident hospitals should be provided to the physician as periodic reports which describe the susceptibility profile of nosocomial and community-acquired pathogens. These reports may differ from susceptibility data obtained from outpatient use, but could aid the physician in selecting the most effective antimicrobial.

Dilution Techniques

Quantitative methods are used to determine antimicrobial minimum inhibitory concentrations (MICs). These MICs provide estimates of the susceptibility of bacteria to antimicrobial compounds. The MICs should be determined using a standardized procedure. Standardized procedures are based on a dilution method^1,3 (broth or agar) or equivalent with standardized inoculum concentrations and standardized concentrations of azithromycin powder. The MIC values should be interpreted according to criteria provided in Table 3.

Diffusion Techniques

Quantitative methods that require measurement of zone diameters also provide reproducible estimates of the susceptibility of bacteria to antimicrobial compounds. One such standardized procedure^2,3 requires the use of standardized inoculum concentrations. This procedure uses paper disks impregnated with 15 mcg azithromycin to test the susceptibility of microorganisms to azithromycin. The disk diffusion interpretive criteria are provided in Table 3.

Table 3. Susceptibility Interpretive Criteria for Azithromycin Susceptibility Test Result Interpretive Criteria

 | Minimum Inhibitory Concentrations (mcg/mL) |  |  | Disk Diffusion; (zone diameters in mm)
Pathogen
 | S | I | Ra | S | I | Ra
Haemophilusinfluenzae | ≤ 4 | - - | - - | ≥ 12 | - - | - -
Staphylococcus aureus | ≤ 2 | 4 | ≥ 8 | ≥ 18 | 14 to 17 | ≤ 13
Streptococcus pneumoniaeb | ≤ 0.5 | 1 | ≥ 2 | ≥ 18 | 14 to 17 | ≤ 13

aThe current absence of data on resistant strains precludes defining any category other than “susceptible”. If strains yield MIC results other than susceptible, they should be submitted to a reference laboratory for further testing.

bSusceptibility of streptococci including, S. pneumoniae to azithromycin and other macrolides can be predicted by testing erythromycin.

No interpretive criteria have been established for testing Neisseria gonorrhoeae. This species is not usually tested.

A report of �susceptible” indicates that the pathogen is likely to be inhibited if the antimicrobial compound reaches the concentrations usually achievable. A report of “intermediate” indicates that the result should be considered equivocal, and, if the microorganism is not fully susceptible to alternative, clinically feasible drugs, the test should be repeated. This category implies possible clinical applicability in body sites where the drug is physiologically concentrated or in situations where high dosage of drug can be used. This category also provides a buffer zone which prevents small uncontrolled technical factors from causing major discrepancies in interpretation. A report of “resistant” indicates that the pathogen is not likely to be inhibited if the antimicrobial compound reaches the concentrations usually achievable; other therapy should be selected.

Quality Control

Standardized susceptibility test procedures require the use of quality control microorganisms to control the technical aspects of the test procedures. Standard azithromycin powder should provide the following range of values noted in Table 4. Quality control microorganisms are specific strains of organisms with intrinsic biological properties. QC strains are very stable strains which will give a standard and repeatable susceptibility pattern. The specific strains used for microbiological quality control are not clinically significant.

Table 4. Acceptable Quality Control Ranges for Azithromycin

QC Strain | Minimum Inhibitory; Concentrations (mcg/mL) | Disk Diffusion; (zone diameters in mm)
Haemophilus influenzae; ATCC 49247 | 1 to 4 | 13 to 21
Staphylococcus aureus; ATCC 29213 | 0.5 to 2
Staphylococcus aureus; ATCC 25923 |  | 21 to 26
Streptococcus pneumoniae; ATCC 49619 | 0.06 to 0.25 | 19 to 25

INDICATIONS AND USAGE

Azithromycin for Injection, USP is indicated for the treatment of patients with infections caused by susceptible strains of the designated microorganisms in the conditions listed below. As recommended dosages, durations of therapy, and applicable patient populations vary among these infections, please see DOSAGE AND ADMINISTRATION for dosing recommendations.

Community-acquired pneumonia due to Chlamydia pneumoniae, Haemophilus influenzae, Legionella pneumophila, Moraxella catarrhalis, Mycoplasma pneumoniae, Staphylococcus aureus, or Streptococcus pneumoniae in patients who require initial intravenous therapy.

Pelvic inflammatory disease due to Chlamydia trachomatis, Neisseria gonorrhoeae, or Mycoplasma hominis in patients who require initial intravenous therapy. If anaerobic microorganisms are suspected of contributing to the infection, an antimicrobial agent with anaerobic activity should be administered in combination with Azithromycin for Injection, USP.

Azithromycin for Injection, USP should be followed by azithromycin by the oral route as required (see DOSAGE AND ADMINISTRATION).

Appropriate culture and susceptibility tests should be performed before treatment to determine the causative microorganism and its susceptibility to azithromycin. Therapy with azithromycin may be initiated before results of these tests are known; once the results become available, antimicrobial therapy should be adjusted accordingly.

To reduce the development of drug-resistant bacteria and maintain the effectiveness of Azithromycin for Injection, USP and other antibacterial drugs, Azithromycin for Injection, USP should be used only to treat or prevent infections that are proven or strongly suspected to be caused by susceptible bacteria. When culture and susceptibility information are available, they should be considered in selecting or modifying antibacterial therapy. In the absence of such data, local epidemiology and susceptibility patterns may contribute to the empiric selection of therapy.

CONTRAINDICATIONS

Azithromycin for Injection is contraindicated in patients with known hypersensitivity to azithromycin, erythromycin, any macrolide or ketolide antibiotic. Azithromycin for Injection is contraindicated in patients with a history of cholestatic jaundice/hepatic dysfunction associated with prior use of azithromycin.

WARNINGS

Hypersensitivity

Serious allergic reactions, including angioedema, anaphylaxis, and dermatologic reactions, including Stevens-Johnson syndrome and toxic epidermal necrolysis have been reported rarely in patients on azithromycin therapy. Although rare, fatalities have been reported (see CONTRAINDICATIONS). Despite initially successful symptomatic treatment of the allergic symptoms, when symptomatic therapy was discontinued, the allergic symptoms recurred soon thereafter in some patients without further azithromycin exposure. These patients required prolonged periods of observation and symptomatic treatment. The relationship of these episodes to the long tissue half-life of azithromycin and subsequent prolonged exposure to antigen is unknown at present.

If an allergic reaction occurs, the drug should be discontinued and appropriate therapy should be instituted. Physicians should be aware that reappearance of the allergic symptoms may occur when symptomatic therapy is discontinued.

Hepatotoxicity

Abnormal liver function, hepatitis, cholestatic jaundice, hepatic necrosis, and hepatic failure have been reported, some of which have resulted in death. Discontinue azithromycin immediately if signs and symptoms of hepatitis occur.

Clostridium difficile-associated diarrhea (CDAD) has been reported with use of nearly all antibacterial agents, including azithromycin for injection, and may range in severity from mild diarrhea to fatal colitis. Treatment with antibacterial agents alters the normal flora of the colon leading to overgrowth of C. difficile.

C. difficile produces toxins A and B which contribute to the development of CDAD. Hypertoxin producing strains of C. difficile cause increased morbidity and mortality, as these infections can be refractory to antimicrobial therapy and may require colectomy. CDAD must be considered in all patients who present with diarrhea following antibiotic use. Careful medical history is necessary since CDAD has been reported to occur over two months after the administration of antibacterial agents.

If CDAD is suspected or confirmed, ongoing antibiotic use not directed against C. difficile may need to be discontinued. Appropriate fluid and electrolyte management, protein supplementation, antibiotic treatment of C. difficile, and surgical evaluation should be instituted as clinically indicated.

QT Prolongation

Prolonged cardiac repolarization and QT interval, imparting a risk of developing cardiac arrhythmia and torsades de pointes, have been seen in treatment with macrolides, including azithromycin. Cases of torsades de pointes have been spontaneously reported during post-marketing surveillance in patients receiving azithromycin. Providers should consider the risk of QT prolongation which can be fatal when weighing the risks and benefits of azithromycin for at-risk groups including:

- patients with known prolongation of the QT interval, a history of torsades de pointes, congenital long QT syndrome, bradyarrhythmias or uncompensated heart failure
- patients on drugs known to prolong the QT interval
- patients with ongoing proarrhythmic conditions such as uncorrected hypokalemia or hypomagnesemia, clinically significant bradycardia, and in patients receiving Class IA (quinidine, procainamide) or Class III (dofetilide, aminodarone, sotalol) antiarrhythmic agents.

Elderly patients may be more susceptible to drug-associated effects on the QT interval.

PRECAUTIONS

General

Because azithromycin is principally eliminated via the liver, caution should be exercised when azithromycin is administered to patients with impaired hepatic function. Due to the limited data in subjects with GFR <10 mL/min, caution should be exercised when prescribing azithromycin in these patients (see CLINICAL PHARMACOLOGY, Special Populations , Renal Insufficiency).

Azithromycin for Injection should be reconstituted and diluted as directed and administered as an intravenous infusion over not less than 60 minutes (see DOSAGE AND ADMINISTRATION).

Local IV site reactions have been reported with the intravenous administration of azithromycin. The incidence and severity of these reactions were the same when 500 mg azithromycin were given over 1 hour (2 mg/mL as 250 mL infusion) or over 3 hours (1 mg/mL as 500 mL infusion) (see ADVERSE REACTIONS). All volunteers who received infusate concentrations above 2 mg/mL experienced local IV site reactions and, therefore, higher concentrations should be avoided.

Exacerbation of symptoms of myasthenia gravis and new onset of myasthenic syndrome have been reported in patients receiving azithromycin therapy.

Prescribing Azithromycin for Injection in the absence of a proven or strongly suspected bacterial infection or a prophylactic indication is unlikely to provide benefit to the patient and increases the risk of the development of drug-resistant bacteria.

Information for Patients

Patients should be directed to discontinue azithromycin and contact a physician if any signs of an allergic reaction occur.

Patients should be counseled that antibacterial drugs including Azithromycin for Injection should only be used to treat bacterial infections. They do not treat viral infections (e.g., the common cold). When Azithromycin for Injection is prescribed to treat a bacterial infection, patients should be told that although it is common to feel better early in the course of the therapy, the medication should be taken exactly as directed. Skipping doses or not completing the full course of therapy may (1) decrease the effectiveness of the immediate treatment and (2) increase the likelihood that bacteria will develop resistance and will not be treatable by Azithromycin for Injection or other antibacterial drugs in the future.

Diarrhea is a common problem caused by antibiotics, which usually ends when the antibiotic is discontinued. Sometimes after starting treatment with antibiotics, patients can develop watery and bloody stools (with or without stomach cramps and fever) even as late as two or more months after having taken the last dose of the antibiotic. If this occurs, patients should contact their physician as soon as possible.

Drug Interactions

Co-administration of nelfinavir at steady-state with a single oral dose of azithromycin resulted in increased azithromycin serum concentrations. Although a dose adjustment of azithromycin is not recommended when administered in combination with nelfinavir, close monitoring for known side effects of azithromycin, such as liver enzyme abnormalities and hearing impairment, is warranted (see ADVERSE REACTIONS).

Although, in a study of 22 healthy men, a 5 day course of azithromycin did not affect the prothrombin time from a subsequently administered dose of warfarin, spontaneous post-marketing reports suggest that concomitant administration of azithromycin may potentiate the effects of oral anticoagulants. Prothrombin times should be carefully monitored while patients are receiving azithromycin and oral anticoagulants concomitantly.

Drug interaction studies were performed with azithromycin and other drugs likely to be co-administered (see CLINICAL PHARMACOLOGY, Drug-Drug Interactions). When used in therapeutic doses, azithromycin had a modest effect on the pharmacokinetics of atorvastatin, carbamazepine, cetirizine, didanosine, efavirenz, fluconazole, indinavir, midazolam, rifabutin, sildenafil, theophylline (intravenous and oral), triazolam, trimethoprim/sulfamethoxazole or zidovudine. Co-administration with efavirenz or fluconazole had a modest effect on the pharmacokinetics of azithromycin. No dosage adjustment of either drug is recommended when azithromycin is co-administered with any of these agents.

Interactions with the drugs listed below have not been reported in clinical trials with azithromycin; however, no specific drug interaction studies have been performed to evaluate potential drug-drug interaction. Nonetheless, they have been observed with macrolide products. Until further data are developed regarding drug interactions when azithromycin and these drugs are used concomitantly, careful monitoring of patients is advised:

Digoxin - elevated digoxin concentrations.

Ergotamine or dihydroergotamine - acute ergot toxicity characterized by severe peripheral vasospasm and dysesthesia.

Terfenadine, cyclosporine, hexobarbital, and phenytoin-elevated concentrations.

Laboratory Test Interactions

There are no reported laboratory test interactions.

Carcinogenesis, Mutagenesis, Impairment of Fertility

Long-term studies in animals have not been performed to evaluate carcinogenic potential. Azithromycin has shown no mutagenic potential in standard laboratory tests: mouse lymphoma assay, human lymphocyte clastogenic assay, and mouse bone marrow clastogenic assay. No evidence of impaired fertility due to azithromycin was found.

Pregnancy

Teratogenic Effects. Pregnancy Category B

Reproduction studies have been performed in rats and mice at doses up to moderately maternally toxic dose concentrations (i.e., 200 mg/kg/day by the oral route). These doses, based on a mg/m^2 basis, are estimated to be 4 and 2 times, respectively, the human daily dose of 500 mg by the oral route. In the animal studies, no evidence of harm to the fetus due to azithromycin was found. There are, however, no adequate and well-controlled studies in pregnant women. Because animal reproduction studies are not always predictive of human response, azithromycin should be used during pregnancy only if clearly needed.

Nursing Mothers

It is not known whether azithromycin is excreted in human milk. Because many drugs are excreted in human milk, caution should be exercised when azithromycin is administered to a nursing woman.

Pediatric Use

Safety and effectiveness of azithromycin for injection in children or adolescents under 16 years have not been established. In controlled clinical studies, azithromycin has been administered to pediatric patients (age 6 months to 16 years) by the oral route. For information regarding the use of azithromycin for oral suspension in the treatment of pediatric patients, refer to the INDICATIONS AND USAGE and DOSAGE AND ADMINISTRATION sections of the prescribing information for azithromycin for oral suspension 100 mg/5 mL and 200 mg/5 mL bottles.

Geriatric Use

Pharmacokinetic studies with intravenous azithromycin have not been performed in older volunteers. Pharmacokinetics of azithromycin following oral administration in older volunteers (65 to 85 years old) were similar to those in younger volunteers (18 to 40 years old) for the 5 day therapeutic regimen.

In multiple-dose clinical trials of intravenous azithromycin in the treatment of community-acquired pneumonia, 45% of patients (188/414) were at least 65 years of age and 22% of patients (91/414) were at least 75 years of age. No overall differences in safety were observed between these subjects and younger subjects in terms of adverse events, laboratory abnormalities, and discontinuations. Similar decreases in clinical response were noted in azithromycin- and comparator-treated patients with increasing age.

Elderly patients may be more susceptible to development of torsades de pointes arrhythmia than younger patients (see WARNINGS).

Azithromycin for Injection contains 114 mg (4.96 mEq) of sodium per vial. At the usual recommended doses, patients would receive 114 mg (4.96 mEq) of sodium. The geriatric population may respond with a blunted natriuresis to salt loading. The total sodium content from dietary and non-dietary sources may be clinically important with regard to such diseases as congestive heart failure.

ADVERSE REACTIONS

In clinical trials of intravenous azithromycin for community-acquired pneumonia, in which 2 to 5 IV doses were given, most of the reported side effects were mild to moderate in severity and were reversible upon discontinuation of the drug. The majority of patients in these trials had one or more co-morbid diseases and were receiving concomitant medications. Approximately 1.2% of the patients discontinued intravenous azithromycin therapy, and a total of 2.4% discontinued azithromycin therapy by either the intravenous or oral route because of clinical or laboratory side effects.

In clinical trials conducted in patients with pelvic inflammatory disease, in which 1 to 2 IV doses were given, 2% of women who received monotherapy with azithromycin and 4% who received azithromycin plus metronidazole discontinued therapy due to clinical side effects.

Clinical side effects leading to discontinuations from these studies were most commonly gastrointestinal (abdominal pain, nausea, vomiting, diarrhea), and rashes; laboratory side effects leading to discontinuation were increases in transaminase levels and/or alkaline phosphatase levels.

Clinical

Overall, the most common side effects associated with treatment in adult patients who received IV/PO azithromycin in studies of community-acquired pneumonia were related to the gastrointestinal system with diarrhea/loose stools (4.3%), nausea (3.9%), abdominal pain (2.7%), and vomiting (1.4%) being the most frequently reported. Approximately 12% of patients experienced a side effect related to the intravenous infusion; most common were pain at the injection site (6.5%) and local inflammation (3.1%).

The most common side effects associated with treatment in adult women who received IV/PO azithromycin in studies of pelvic inflammatory disease were related to the gastrointestinal system. Diarrhea (8.5%) and nausea (6.6%) were most commonly reported, followed by vaginitis (2.8%), abdominal pain (1.9%), anorexia (1.9%), rash and pruritus (1.9%). When azithromycin was co-administered with metronidazole in these studies, a higher proportion of women experienced side effects of nausea (10.3%), abdominal pain (3.7%), vomiting (2.8%), application site reaction, stomatitis, dizziness, or dyspnea (all at 1.9%).

No other side effects occurred in patients on the multiple-dose IV/PO regimen of azithromycin in these studies with a frequency greater than 1%.

Side effects that occurred with a frequency of 1% or less included the following:

Gastrointestinal: dyspepsia, flatulence, mucositis, oral moniliasis, and gastritis.

Nervous System: headache, somnolence.

Allergic: bronchospasm.

Special Senses: taste perversion.

Post-Marketing Experience

Adverse events reported with azithromycin during the post-marketing period in adult and/or pediatric patients for which a causal relationship may not be established include:

Allergic: arthralgia, edema, urticaria and angioedema.

Cardiovascular: arrhythmias including ventricular tachycardia and hypotension. There have been rare reports of QT prolongation and torsades de pointes.

Gastrointestinal: anorexia, constipation, dyspepsia, flatulence, vomiting/diarrhea rarely resulting in dehydration, pseudomembranous colitis, pancreatitis, oral candidiasis, pyloric stenosis and rare reports of tongue discoloration.

General: asthenia, paresthesia, fatigue, malaise and anaphylaxis (rarely fatal).

Genitourinary: interstitial nephritis and acute renal failure and vaginitis.

Hematopoietic: thrombocytopenia.

Liver/Biliary: adverse reactions related to hepatic dysfunction have been reported in post-marketing experience with azithromycin (see WARNINGS , Hepatotoxicity).

Nervous System: convulsions, dizziness/vertigo, headache, somnolence, hyperactivity, nervousness, agitation and syncope.

Psychiatric: aggressive reaction and anxiety.

Skin/Appendages: pruritus, rarely serious skin reactions including erythema multiforme, Stevens-Johnson syndrome and toxic epidermal necrolysis.

Special Senses: hearing disturbances including hearing loss, deafness and/or tinnitus and reports of taste/smell perversion and/or loss.

Laboratory Abnormalities

Significant abnormalities (irrespective of drug relationship) occurring during the clinical trials were reported as follows:

with an incidence of 4 to 6%, elevated ALT (SGPT), AST (SGOT), creatinine

with an incidence of 1 to 3%, elevated LDH, bilirubin

with an incidence of less than 1%, leukopenia, neutropenia, decreased platelet count, and elevated serum alkaline phosphatase

When follow-up was provided, changes in laboratory tests appeared to be reversible.

In multiple-dose clinical trials involving more than 750 patients treated with azithromycin (IV/PO), less than 2% of patients discontinued azithromycin therapy because of treatment-related liver enzyme abnormalities.

DOSAGE AND ADMINISTRATION

(See INDICATIONS AND USAGE and CLINICAL PHARMACOLOGY.)

The recommended dose of Azithromycin for Injection for the treatment of adult patients with community-acquired pneumonia due to the indicated organisms is: 500 mg as a single daily dose by the intravenous route for at least two days. Intravenous therapy should be followed by azithromycin by the oral route at a single, daily dose of 500 mg, administered as two 250 mg tablets to complete a 7 to 10 day course of therapy. The timing of the switch to oral therapy should be done at the discretion of the physician and in accordance with clinical response.

The recommended dose of Azithromycin for Injection for the treatment of adult patients with pelvic inflammatory disease due to the indicated organisms is: 500 mg as a single daily dose by the intravenous route for one or two days. Intravenous therapy should be followed by azithromycin by the oral route at a single, daily dose of 250 mg to complete a 7 day course of therapy. The timing of the switch to oral therapy should be done at the discretion of the physician and in accordance with clinical response. If anaerobic microorganisms are suspected of contributing to the infection, an antimicrobial agent with anaerobic activity should be administered in combination with Azithromycin for Injection.

Renal Insufficiency

No dosage adjustment is recommended for subjects with renal impairment (GFR ≤80 mL/min). The mean AUC0-120 was similar in subjects with GFR 10 to 80 mL/min compared to subjects with normal renal function, whereas it increased 35% in subjects with GFR <10 mL/min compared to subjects with normal renal function. Caution should be exercised when azithromycin is administered to subjects with severe renal impairment (see CLINICAL PHARMACOLOGY, Special Populations , Renal Insufficiency).

Hepatic Insufficiency

The pharmacokinetics of azithromycin in subjects with hepatic impairment have not been established. No dose adjustment recommendations can be made in patients with impaired hepatic function (see CLINICAL PHARMACOLOGY, Special Populations, Hepatic Insufficiency).

No dosage adjustment is recommended based on age or gender (see CLINICAL PHARMACOLOGY, Special Populations).

The infusate concentration and rate of infusion for Azithromycin for Injection should be either 1 mg/mL over 3 hours or 2 mg/mL over 1 hour. Azithromycin for Injection should not be given as a bolus or as an intramuscular injection.

Preparation of the solution for intravenous administration is as follows:

Reconstitution

Prepare the initial solution of Azithromycin for Injection by adding 4.8 mL of Sterile Water for Injection to the 500 mg vial and shaking the vial until all of the drug is dissolved. Since Azithromycin for Injection is supplied under vacuum, it is recommended that a standard 5 mL (non-automated) syringe be used to ensure that the exact amount of 4.8 mL of Sterile Water is dispensed. Each mL of reconstituted solution contains 100 mg azithromycin. Reconstituted solution is stable for 24 hours when stored below 30°C (86°F).

Parenteral drug products should be inspected visually for particulate matter prior to administration. If particulate matter is evident in reconstituted fluids, the drug solution should be discarded.

Dilute this solution further prior to administration as instructed below.

Dilution

To provide azithromycin over a concentration range of 1 to 2 mg/mL, transfer 5 mL of the 100 mg/mL azithromycin solution into the appropriate amount of any of the diluents listed below:

Normal Saline (0.9% sodium chloride)

1/2 Normal Saline (0.45% sodium chloride)

5% Dextrose in Water

Lactated Ringer’s Solution

5% Dextrose in 1/2 Normal Saline (0.45% sodium chloride) with 20 mEq KCl

5% Dextrose in Lactated Ringer’s Solution

5% Dextrose in 1/3 Normal Saline (0.3% sodium chloride)

5% Dextrose in 1/2 Normal Saline (0.45% sodium chloride)

Normosol®-M in 5% Dextrose

Normosol®-R in 5% Dextrose

Final Infusion Solution

Concentration (mg/mL) Amount of Diluent (mL)

1 mg/mL 500 mL

2 mg/mL 250 mL

It is recommended that a 500 mg dose of Azithromycin for Injection, diluted as above, be infused over a period of not less than 60 minutes.

Azithromycin for Injection should not be given as a bolus or as an intramuscular injection.

Other intravenous substances, additives, or medications should not be added to Azithromycin for Injection or infused simultaneously through the same intravenous line.

Storage

Store the white to off-white lyophilized cake at 20° to 25°C (68° to 77°F) [see USP Controlled Room Temperature]. When diluted according to the instructions (1 mg/mL to 2 mg/mL), Azithromycin for Injection is stable for 24 hours at or below room temperature 30°C (86°F), or for 7 days if stored under refrigeration 5°C (41°F).

HOW SUPPLIED

Azithromycin for Injection, USP is supplied in lyophilized form under a vacuum in a 10 mL vial equivalent to 500 mg of azithromycin for intravenous administration. Each vial also contains sodium hydroxide and 413.6 mg citric acid.

Product; No. | NDC; No.
NP309810 | 63323-398-12 | Packaged in tens

This container closure is not made with natural rubber latex.

CLINICAL STUDIES

Community-Acquired Pneumonia

In a controlled study of community-acquired pneumonia performed in the U.S., azithromycin (500 mg as a single daily dose by the intravenous route for 2 to 5 days, followed by 500 mg/day by the oral route to complete 7 to 10 days therapy) was compared to cefuroxime (2250 mg/day in three divided doses by the intravenous route for 2 to 5 days followed by 1000 mg/day in two divided doses by the oral route to complete 7 to 10 days therapy), with or without erythromycin. For the 291 patients who were evaluable for clinical efficacy, the clinical outcome rates, i.e., cure, improved, and success (cure + improved) among the 277 patients seen at 10 to 14 days post-therapy were as follows:

Clinical Outcome | Azithromycin | Comparator
Cure | 46% | 44%
Improved | 32% | 30%
Success (Cure + Improved) | 78% | 74%

In a separate, uncontrolled clinical and microbiological trial performed in the U.S., 94 patients with community-acquired pneumonia who received azithromycin in the same regimen were evaluable for clinical efficacy. The clinical outcome rates, i.e., cure, improved, and success (cure + improved) among the 84 patients seen at 10 to 14 days post-therapy were as follows:

Clinical Outcome | Azithromycin
Cure | 60%
Improved | 29%
Success (Cure + Improved) | 89%

Microbiological determinations in both trials were made at the pre-treatment visit and, where applicable, were reassessed at later visits. Serological testing was done on baseline and final visit specimens. The following combined presumptive bacteriological eradication rates were obtained from the evaluable groups:

Combined Bacteriological Eradication Rates for Azithromycin:

(at last completed visit) | Azithromycin
S. pneumoniae | 64/67 (96%)a
H. influenzae | 41/43 (95%)
M. catarrhalis | 9/10
S. aureus | 9/10

a Nineteen of twenty-four patients (79%) with positive blood cultures for S. pneumoniae were cured (intent-to-treat analysis) with eradication of the pathogen.

The presumed bacteriological outcomes at 10 to 14 days post-therapy for patients treated with azithromycin with evidence (serology and/or culture) of atypical pathogens for both trials were as follows:

Evidence of Cure +

Infection Total Cure Improved Improved

Mycoplasma pneumoniae 18 11 (61%) 5 (28%) 16 (89%)

Chlamydia pneumoniae 34 15 (44%) 13 (38%) 28 (82%)

Legionella pneumophila 16 5 (31%) 8 (50%) 13 (81%)

ANIMAL TOXICOLOGY

Phospholipidosis (intracellular phospholipid accumulation) has been observed in some tissues of mice, rats, and dogs given multiple doses of azithromycin. It has been demonstrated in numerous organ systems (e.g., eye, dorsal root ganglia, liver, gallbladder, kidney, spleen, and pancreas) in dogs treated with azithromycin at doses which, expressed on the basis of mg/m^2, are approximately equal to the recommended adult human dose, and in rats treated at doses approximately one-sixth of the recommended adult human dose. This effect has been shown to be reversible after cessation of azithromycin treatment. Phospholipidosis has been observed to a similar extent in the tissues of neonatal rats and dogs given daily doses of azithromycin ranging from 10 days to 30 days. Based on the pharmacokinetic data, phospholipidosis has been seen in the rat (30 mg/kg dose) at observed Cmax value of 1.3 mcg/mL (six times greater than the observed Cmax of 0.216 mcg/mL at the pediatric dose of 10 mg/kg). Similarly, it has been shown in the dog (10 mg/kg dose) at observed Cmax value of 1.5 mcg/mL (seven times greater than the observed same Cmax and drug dose in the studied pediatric population). On a mg/m^2 basis, 30 mg/kg dose in the neonatal rat (135 mg/m^2) and 10 mg/kg dose in the neonatal dog (79 mg/m^2) are approximately 0.45 and 0.3 times, respectively, the recommended dose in the pediatric patients with an average body weight of 25 kg. Phospholipidosis, similar to that seen in the adult animals, is reversible after cessation of azithromycin treatment. The significance of these findings for animals and for humans is unknown.

REFERENCES

1. Clinical and Laboratory Standards Institute. Performance Standards for Antimicrobial Susceptibility Testing; 21st Informational Supplement. CLSI document M100-S21. (ISBN 1-56238-742-1). CLSI, 940 West Valley Road, Suite 1400, Wayne, PA, 19087-1898 USA. 2011.
2. Clinical and Laboratory Standards Institute. Methods for Dilution Antimicrobial Susceptibility Tests for Bacteria that Grow Aerobically; Approved Standard – 8th ed. CLSI document M07-A8. (ISBN 1-56238-689-1). CLSI, 940 West Valley Road, Suite 1400, Wayne, PA, 19087-1898 USA. 2009.
3. Clinical and Laboratory Standards Institute. Performance Standards for Antimicrobial Disk Susceptibility Tests; Approved Standard – 10th ed. CLSI document M02-A10. (ISBN 1-56238-688-3). CLSI, 940 West Valley Road, Suite 1400, Wayne, PA, 19087-1898 USA. 2009.

The brand names mentioned in this document are the trademarks of their respective owners.

N+ and NOVAPLUS are registered trademarks of Novation, LLC.

Manufactured by:

Fresenius Kabi USA, LLC

Lake Zurich, IL 60047

451064E/Revised: April 2013

PACKAGE LABEL

PACKAGE LABEL - PRINCIPAL DISPLAY - Azithromycin 500 mg Vial Label

NDC 63323-398-12

NP309810

Azithromycin for Injection, USP

For IV infusion only

500 mg/vial

Rx only

PACKAGE LABEL - PRINCIPAL DISPLAY - Azithromycin 500 mg Vial Tray Label

NDC 63323-398-12

NP309810

Azithromycin for Injection, USP

For IV infusion only

500 mg/vial

To yield 100 mg/mL of solution when reconstituted as directed.

10 vials

Rx only